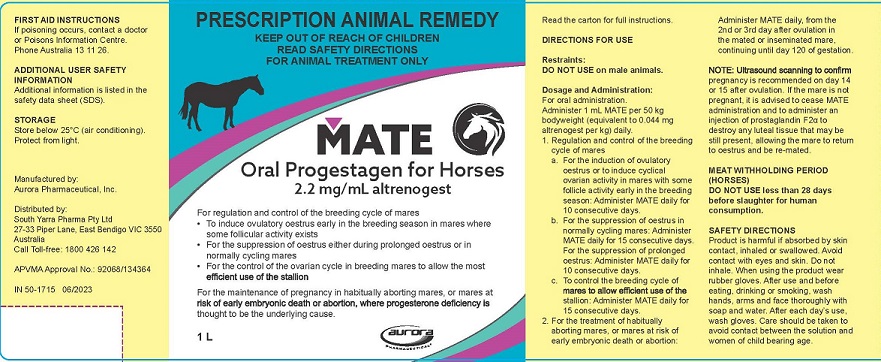 DRUG LABEL: Mate
NDC: 51072-119 | Form: SOLUTION
Manufacturer: Aurora Pharmaceutical, Inc.
Category: animal | Type: PRESCRIPTION ANIMAL DRUG LABEL
Date: 20230906

ACTIVE INGREDIENTS: ALTRENOGEST 2.2 mg/1 mL

Mate Oral Progestagen for Horses

DOSAGE FORMS AND STRENGTHS

2.2 mg/mL altrenogest

VETERINARY INDICATIONS

For regulation and control of the breeding cycle of mares
• To induce ovulatory oestrus early in the breeding season in mares where some follicular activity exists
• For the suppression of oestrus either during prolonged oestrus or in normally cycling mares
• For the control of the ovarian cycle in breeding mares to allow the most efficient use of the stallion

For the maintenance of pregnancy in habitually aborting mares, or mares at risk of early embryonic death or abortion, where progesterone deficiency is thought to be the underlying cause.

CONTRAINDICATIONS

Read the carton for full instruction

DIRECTIONS FOR USE

Restraints:
DO NOT USE on male animals.

Contraindications:
Contraindicated for use in mares suffering from uterine infections.

Precautions:
Use with caution as unused feed must be destroyed and not given to any other animals.
MATE must be added to the feed immediately prior to consumption and not stored.

Dosage and Administration:

For oral administration.
Administer 1 mL MATE per 50 kg bodyweight (equivalent to 0.044 mg altrenogest per kg) daily.
1. Regulation and control of the breeding cycle of mares
a. For the induction of ovulatory oestrus or to induce cyclical ovarian activity in mares with some follicle activity early in the breeding season: Administer MATE daily for 10 consecutive days.
b. For the suppression of oestrus in normally cycling mares: Administer MATE daily for 15 consecutive days. For the suppression of prolonged oestrus: Administer MATE daily for 10 consecutive days.
c. To control the breeding cycle of mares to allow efficient use of the stallion: Administer MATE daily for 15 consecutive days.
2. For the treatment of habitually aborting mares, or mares at risk of early embryonic death or abortion: Administer MATE daily, from the 2nd or 3rd day after ovulation in the mated or inseminated mare, continuing until day 120 of gestation.

NOTE: Ultrasound scanning to confirm pregnancy is recommended on day 14 or 15 after ovulation. If the mare is not pregnant, it is advised to cease MATE administration and to administer an injection of prostaglandin F2α to destroy any luteal tissue that may be still present, allowing the mare to return to oestrus and be re-mated.

MEAT WITHHOLDING PERIODS (HORSES)

DO NOT USE less than 28 days before slaughter for human consumption.

SAFETY DIRECTIONS

Product is harmful if absorbed by skin contact, inhaled or swallowed. Avoid contact with eyes and skin. Do not inhale. When using the product wear rubber gloves. After use and before eating, drinking or smoking, wash hands, arms and face thoroughly with soap and water. After each day's use, wash gloves. Care should be taken to avoid contact between the solution and women of child bearing age.

FIRST AID INSTRUCTIONS
If poisoning occurs, contact a doctor or Poisons Information Centre. Phone Australia 13 11 26.

ADDITIONAL USER SAFETY INFORMATION
Additional information is listed in the safety data sheet (SDS).

STORAGE

Store below 25°C (air conditioning). Protect from light.

Manufactured by:
Aurora Pharmaceutical, Inc.

Distributed by:
South Yarra Pharma Pty Ltd
27-33 Piper Line, East Bendigo VIC 3550
Australia
Call Toll-free: 1800 426 142

APVMA Approval No.: 92068/134364

PRINCIPAL DISPLAY PANEL - 1000 mL bottle label

IN 50-1715 06/2023